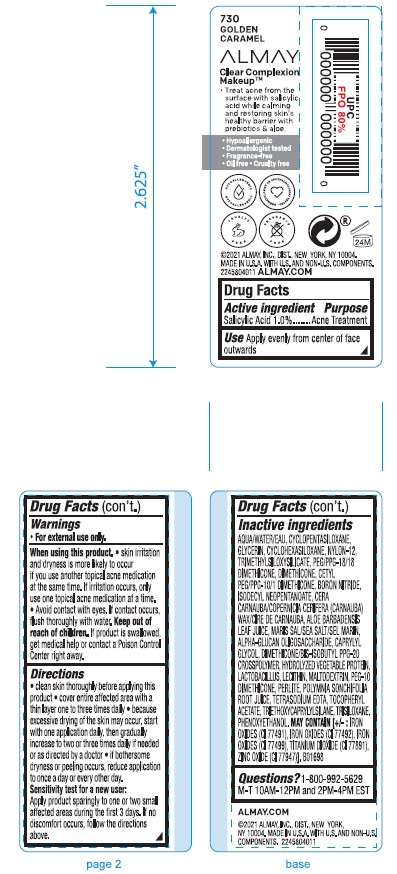 DRUG LABEL: ALMAY CLEAR COMPLEXION MAKEUP FOUNDATION
NDC: 0311-0758 | Form: EMULSION
Manufacturer: ALMAY
Category: otc | Type: HUMAN OTC DRUG LABEL
Date: 20241231

ACTIVE INGREDIENTS: SALICYLIC ACID 1 mg/1 mL
INACTIVE INGREDIENTS: SODIUM BENZOATE; POTASSIUM SORBATE; HYDROLYZED CORN PROTEIN (ENZYMATIC; 1500 MW); POLYMNIA SONCHIFOLIA ROOT JUICE; ISODECYL NEOPENTANOATE; LACTOBACILLUS; ALOE VERA LEAF; WATER; CAPRYLYL GLYCOL; CYCLOPENTASILOXANE; DIMETHICONE; GLYCERIN; DIMETHICONE/BIS-ISOBUTYL PPG-20 CROSSPOLYMER; FERRIC OXIDE RED; FERRIC OXIDE YELLOW; PEG/PPG-18/18 DIMETHICONE; PEG-10 DIMETHICONE (600 CST); PHENOXYETHANOL; TETRASODIUM EDTA; ALPHA-TOCOPHEROL ACETATE; TRIMETHYLSILOXYSILICATE (M/Q 0.6-0.8); TITANIUM DIOXIDE; CETYL PEG/PPG-10/1 DIMETHICONE (HLB 2); CYCLOHEXASILOXANE; CARNAUBA WAX; PERLITE; .ALPHA.-GLUCAN OLIGOSACCHARIDE; BORON NITRIDE; SEA SALT; NYLON-12; TRIETHOXYCAPRYLYLSILANE; ZINC OXIDE; MALTODEXTRIN; TRISILOXANE; FERROSOFERRIC OXIDE; LECITHIN, SOYBEAN

ALMAY CLEAR COMPLEXION MAKEUP FOUNDATION - BUFF

ACTIVE INGREDIENT

Salicylic Acid 1.0%

PURPOSE

Acne Treatment

USE

Helps clear and prevent new acne blemishes

WARNINGS

For external use only.
When using this product
• Skin irritation and dryness is more likely to occur if you use another topical acne mediation at the same time. If irritation occurs, only use one topical acne medication at a time.
• Avoid contact with eyes. If contact occurs, flush thoroughly with water

WARNINGS

• Keep out of reach of children. If product is swallowed, get medical help or
contact a poison control center right away.

DIRECTIONS

Apply evenly from center of face outwards.
• clean skin thoroughly before applying this product.
• cover entire affected area with a thin layer one to three times daily
• because excessive drying of the skin may occur, start with one application daily, then gradually increase to two to three times daily if needed or as directed by a doctor.
• if bothersome dryness or peeling occurs, reduce application to once a day or every other day.
Sensitivity test for a new user:
Apply product sparingly to one or two small affected areas during the first 3 days. If no discomfort occurs, follow the directions above.

OTHER INGREDIENTS

Other ingredients AQUA/WATER/EAU, CYCLOPENTASILOXANE, GLYCERIN, CYCLOHEXASILOXANE, NYLON-12,
TRIMETHYLSILOXYSILICATE, PEG/PPG-18/18 DIMETHICONE, DIMETHICONE, CETYL PEG/PPG-10/1 DIMETHICONE, BORON NITRIDE, ISODECYL NEOPENTANOATE, CERA CARNAUBA/COPERNICIA CERIFERA (CARNAUBA) WAX/CIRE DE CARNAUBA, ALOE BARBADENSIS LEAF JUICE, MARIS SAL/SEA SALT/SEL MARIN, ALPHA-GLUCAN OLIGOSACCHARIDE, CAPRYLYL GLYCOL, DIMETHICONE/BIS-ISOBUTYL PPG-20 CROSSPOLYMER, HYDROLYZED VEGETABLE PROTEIN, LACTOBACILLUS, LECITHIN, MALTODEXTRIN, PEG-10 DIMETHICONE, PERLITE, POLYMNIA SONCHIFOLIA ROOT JUICE, TETRASODIUM EDTA, TOCOPHERYL ACETATE, TRIETHOXYCAPRYLYLSILANE, TRISILOXANE, PHENOXYETHANOL
MAY CONTAIN/PEUT CONTENIR/PUEDE CONTENER (+/-):
[IRON OXIDES (CI 77491), IRON OXIDES (CI 77492), IRON OXIDES (CI 77499), TITANIUM DIOXIDE (CI 77891), ZINC OXIDE (CI 77947).